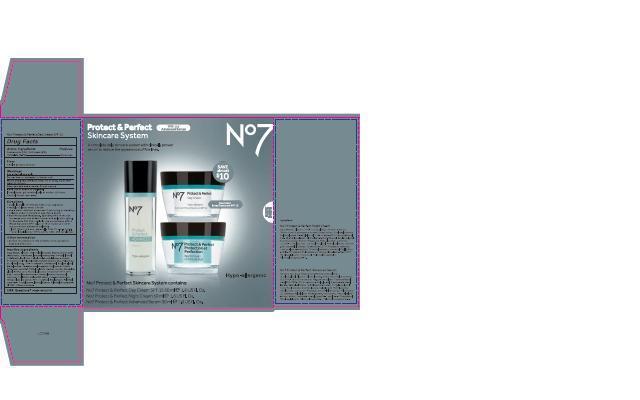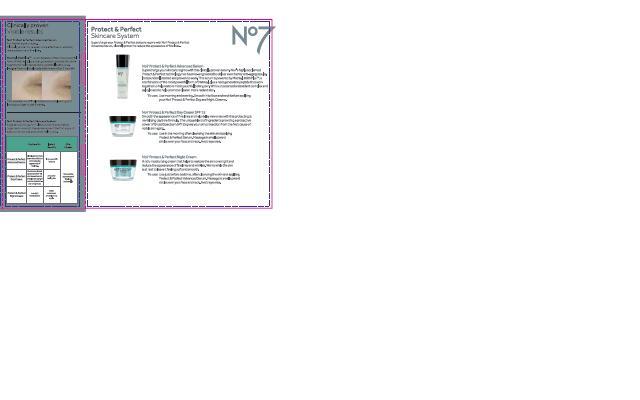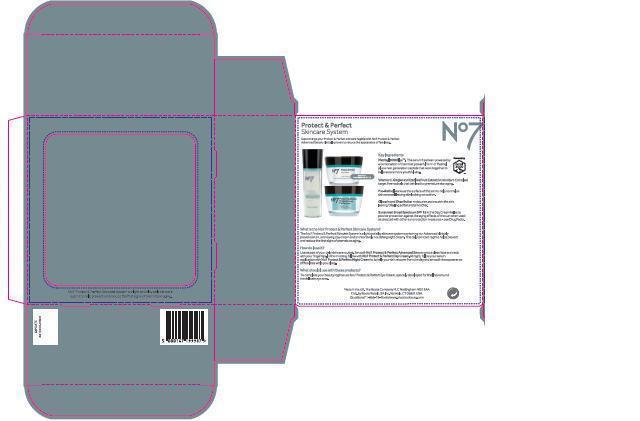 DRUG LABEL: No7 Protect and Perfect Day Cream SPF 15
NDC: 11489-086 | Form: CREAM
Manufacturer: BCM Ltd
Category: otc | Type: HUMAN OTC DRUG LABEL
Date: 20140822

ACTIVE INGREDIENTS: AVOBENZONE 1.5 g/50 g; OCTOCRYLENE 2 g/50 g; OCTISALATE 1 g/50 g
INACTIVE INGREDIENTS: WATER; GLYCERIN; C12-15 ALKYL BENZOATE; DIMETHICONE; PHENOXYETHANOL; ALCOHOL; SHEA BUTTER; POTASSIUM CETYL PHOSPHATE; BUTYLENE GLYCOL; METHYLPARABEN; ETHYLPARABEN; XANTHAN GUM; DIPROPYLENE GLYCOL; VITAMIN A PALMITATE; ASCORBYL GLUCOSIDE; ALFALFA; EDETATE SODIUM; LUPINUS ALBUS SEED; PHYLLANTHUS EMBLICA FRUIT; POTASSIUM HYDROXIDE; GINKGO BILOBA LEAF OIL; TOCOPHEROL; PALMITOYL OLIGOPEPTIDE; PALMITOYL TETRAPEPTIDE-7; ISONONYL ISONONANOATE; POLYGLYCERYL-3 DIISOSTEARATE; POLYACRYLAMIDE (1500 MW); MICA; LAURETH-7; SUCROSE COCOATE; CITRIC ACID ACETATE; BUTYLPARABEN; PROPYLPARABEN; ISOBUTYLPARABEN; TITANIUM DIOXIDE; BUTYLATED HYDROXYTOLUENE

No7 Protect and Perfect Day Cream SPF 15

Carton Active Ingredients Section

Active ingredients

Avobenzone 3%

Octisalate 2%

Octocrylene 4%

Uses

Uses - helps prevent sunburn

Warnings

For external use only

Do not use on damaged or broken skin

When using this product keep out of eyes. Rinse with water to remove.

Ask a doctor

Stop use and ask a doctor if rash occurs

Keep out of reach of children

If swallowed, get medical help or contact a Poison Control Center right away

Directions

Apply liberally 15 minutes before sun exposure

reapply at least every 2 hours

use a water resistnat sunscreen if swimming or sweating

children under 6 months of age: Ask a doctor

Sun Protection Measures. Spending time in the sun increases your risk of skin cancer and early skin aging.

To decrease this risk, regularly use a sunscreen with a Broad Spectrum SPF value of 15 or higher and other sun protection measures including:

Limit time in the sun, especially from 10 a.m - 2 p.m.

wear long-sleeved shirts,pants,hats and sunglasses.

Storage

Other information

Protect the product in this container from excessive heat and direct sun

Inactive ingredients

Aqua(Water), Glycerin, C12-15 alkyl benzoate, Butyrospermum parkii (Shea) butter, Dimethicone, Isononyl isononanoate, C18-36 acid glycol ester, Cetearyl alcohol, Polyglyceryl-3 methylglucose distearate, Phenoxyethanol, Polyacrylamide, Sorbitan stearate, Mica, Polysorbate-20, Alcohol denat., C13-14 isoparaffin, Dimethiconol, Butylene glycol, Methylparaben, Potassium cetyl phosphate, Ethylparaben, Parfum(Fragrance), Laureth-7, Retinyl palmitate, Sucrose cocoate, Dipropylene glycol, Ascorbyl glucoside, Xanthan gum, Tetrasodium EDTA, Citric acid, Lupinus albus seed extract, Dimethylmethoxy chromanol, Carbomer, Phyllanthus emblica fruit extract, Potassium hydroxide, Ginkgo biloba leaf extract, BHT, Tocopherol, Butylparaben, Palmitoyl oligopepetide, Propylparaben, Isobutylparaben, Palmitoyl tetrapeptide-7, CI 77891.

PATIENT COUNSELING INFORMATION

Made in the UK

The Boots Company PLC Nottingham England NG2 3AA

Dist. by Boots Retail USA Inc. Norwalk CT 06851 USA

www.boots.com

Description

The No7 Protect and Perfect Skincare System is a light and silky skincare system containing our Advanced clinically proven serum, a renewing day cream and an intensively nourishing night cream. This daily skincare regime helps prevent and reduce the first signs of premature aging.

How do I use it?

Use as part of your daily skincare routine. Smooth No7 Protect and Perfect Advanced Serum onto a clean face and neck with your finger tips. In the morning, follow with No7 Protect and Perfect Day Cream. At night, follow your serum application with No7 Protect & Perfect Night Cream to help your skin recover from the day and smooth the appearance of fine lines while you sleep.

What should I use with these products?

To complete your beauty regime use No7 Protect and Perfect Eye Cream, specially developed for fine lines around the delicate eye area.

Description

Protect and Perfect Skincare System.

Supercharge your Protect and Perfect skincare regime with No7 Protect and Perfect Advanced Serum, clinically proven to reduce the appearance of fine lines.

No7 Protect and Perfect Advanced Serum.

Supercharge your skincare regime with this clinically proven serum. No7's highly acclaimed Protect and Perfect technology has been re-engineered to deliver even better anti-aging results. Independently tested and proven to work. This serum is powered by Matrixyl 3000 Plus T, a combination of the most powerful form of Matrixyl, plus a next generation peptide that work together to help restore more youthfu looking skin. With our patented antioxidant complex and salicylic acid to help promote clearer,more radiant skin.

To use: Use morning and evening. Smooth into face and neck befoe applying your Protect and Perfect Day and Night Creams.

No7 Protect and Perfect Day Cream SPF 15. Smooth the appearance of fine lines and help delay new ones with this protecting and revitalising daytime formula. The unique blend of ingredients providing a protective power of Broad Spectrum SPF15 gives your skin protection from the No1 cause of visible skin aging.

To use: Use in the morning after cleansing the skin and applying Protect and Perfect Serum. Massage in small upward circles over your face and neck. Avoid eye area.

No7 Protect and Perfect Night Cream

A rich moisturising cream that helps to restore the skin overnight and reduce the appearance of fine lines and wrinkles. works while the skin is at rest to leave it feeling soft and smooth.

To use: Use just before bedtime, after cleansing the skin and applying Protect and Perfect Advanced Serum. Massge in small upward circles over your face and neck. Avoid eye area.